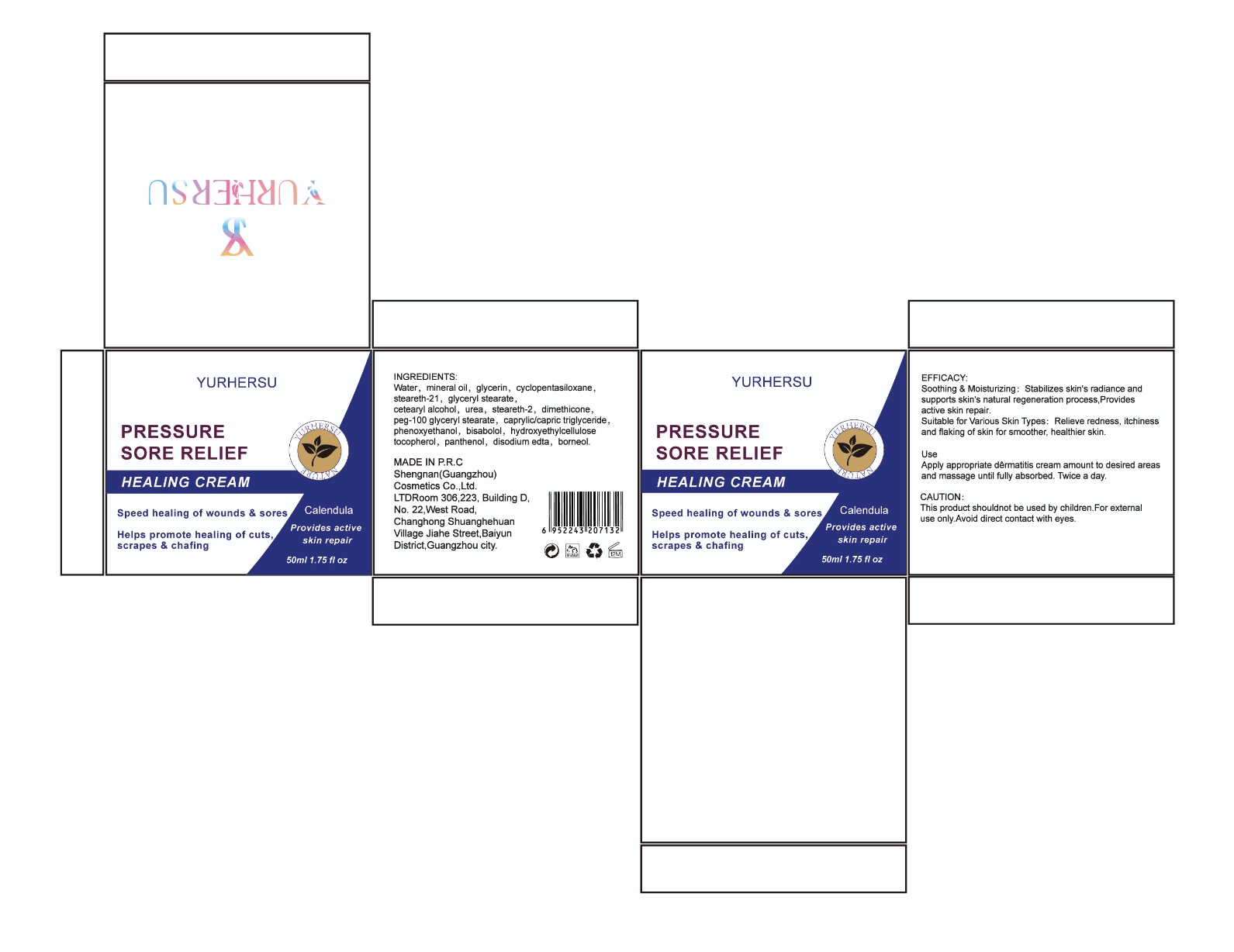 DRUG LABEL: Healing Cream
NDC: 84019-002 | Form: CREAM
Manufacturer: Shengnan (Guangzhou) Cosmetics Co., LTD
Category: otc | Type: HUMAN OTC DRUG LABEL
Date: 20240523

ACTIVE INGREDIENTS: BORNEOL 2 g/100 mL
INACTIVE INGREDIENTS: DODECANEDIOIC ACID; CETYL HYDROXYETHYLCELLULOSE (350000 MW); TOCOPHEROL; DIMETHICONE CROSSPOLYMER (450000 MPA.S AT 12% IN CYCLOPENTASILOXANE); .BETA.-BISABOLOL; STEARETH-2; STEARETH-21; MINERAL OIL; PANTHENOL; PEG-100 STEARATE; GLYCERIN; PHENOXYETHANOL; DIMETHICONE; DISODIUM EDTA-COPPER; GLYCERYL STEARATE SE; CAPRYLIC ACID; WATER; (4-(TRIFLUOROMETHOXY)PHENYL)UREA

HEALING CREAM

ACTIVE INGREDIENT

borneol 2%

Purpose

Helps promote healing of cuts.scrapes &chafing

Warnings

This product shouldnot be used by children.For externaluse only.Avoid direct contact with eyes

Stop use and ask a doctor if

rash occurs

Do not use

Appearing allergic conditions

When using this product

keep out of eyes: Rinse with water to remove

Keep out of reach of children.

If swallowed, get medical help or contact a Poison Control Center right away.

INACTIVE INGREDIENT

Water
mineral oil

glycerin
cyclopentasiloxane

steareth-21
glyceryl stearate
cetearyl alcohol
urea

steareth-2

dimethicone

peg-100 glyceryl stearate

caprylic
phenoxyethanol

bisabolol

hydroxyethylcellulos

tocopherol

panthenol

disodium edta

DOSAGE AND ADMINISTRATION

Apply appropriate dêrmatitis cream amount to desired areasand massage until fully absorbed. Twice a day.

INDICATIONS AND USAGE

Apply appropriate dêrmatitis cream amount to desired